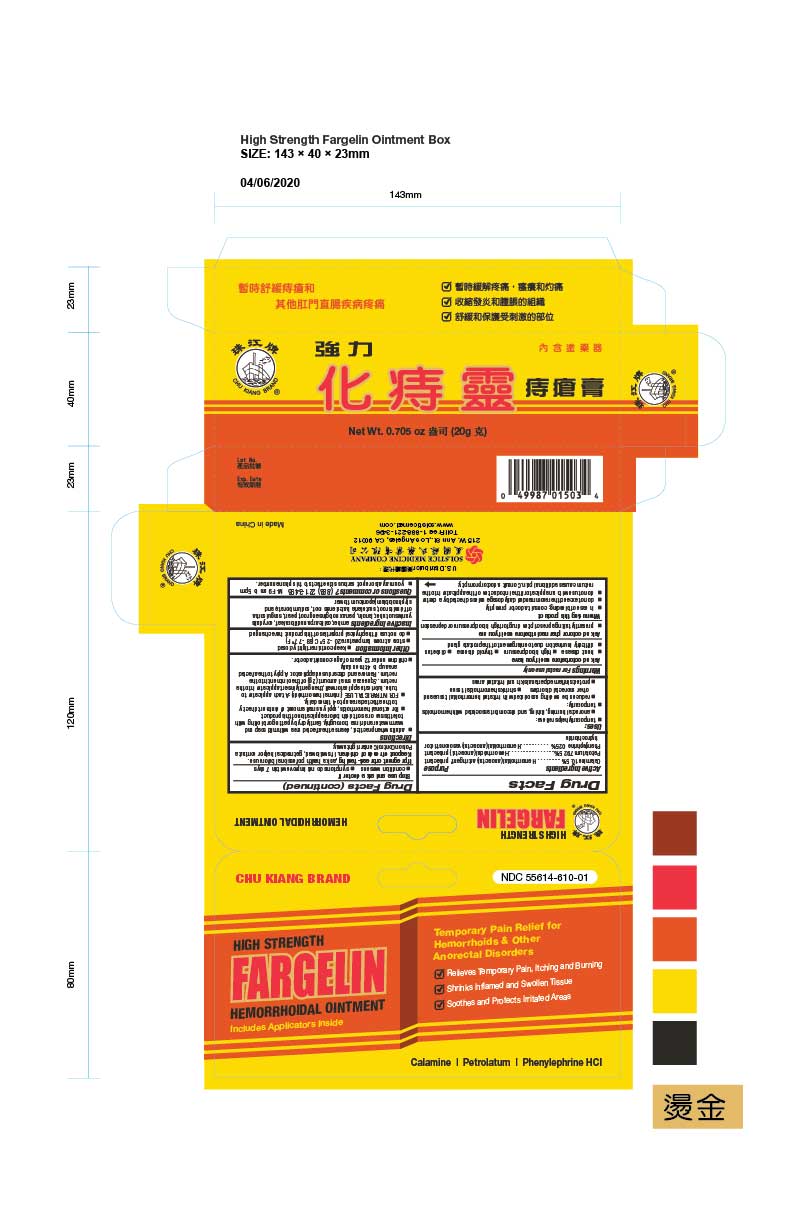 DRUG LABEL: FARGELIN HEMORRHOIDAL
NDC: 55614-610 | Form: OINTMENT
Manufacturer: MADISON ONE ACME INC
Category: otc | Type: HUMAN OTC DRUG LABEL
Date: 20251110

ACTIVE INGREDIENTS: ZINC OXIDE 10.3 g/100 g; FERRIC OXIDE RED 0.05 g/100 g; PETROLATUM 79.25 g/100 g; PHENYLEPHRINE HYDROCHLORIDE 0.25 g/100 g
INACTIVE INGREDIENTS: AMBER; CALLICARPA NUDIFLORA LEAF; CORYDALIS YANHUSUO TUBER; LANOLIN; PANAX NOTOGINSENG ROOT; PEARL (HYRIOPSIS CUMINGII); SANGUISORBA OFFICINALIS ROOT; SCUTELLARIA BAICALENSIS ROOT; SODIUM BORATE; STYPHNOLOBIUM JAPONICUM FLOWER

Drug Facts

Active ingredients
Calamine 10.5%
Petrolatum 79.25%
Phenylephrine hydrochloride 0.25%

Purpose
Hemorrhoidal (anorectal) astringent/protectant
Hemorrhoidal (anorectal) protectant
Hemorrhoidal (anorectal) vasoconstrictor

Uses
temporarily helps relieve:
anorectal burning, itching, and discomfort associated with hemorrhoids
temporarily:
reduces the swelling associated with irritated hemorrhoidal tissue and other anorectal disorders
shrinks hemorrhoidal tissue
protects inflamed perianal skin and irritated areas

Warnings
For rectal use only

Ask a doctor before use if you have
heart disease
high blood pressure
thyroid disease
diabetes
difficulty in urination due to enlargement of the prostate gland

Ask a doctor or pharmacist before use if you are
presently taking a prescription drug for high blood pressure or depression

When using this product
in case of bleeding; consult a doctor promptly
do not exceed the recommended daily dosage unless directed by a doctor
do not use with an applicator if the introduction of the applicator into the rectum causes additional pain. Consult a doctor promptly.

Stop use and ask a doctor if
condition worsens
symptoms do not improve within 7 days

PREGNANCY OR BREAST FEEDING

If pregnant or breast-feeding,ask a health professional before use.

Keep out of reach of children.If swallowed, get medical help or contact a Poison Control Center right away.

Directions

- adults: when practical, cleanse the affected area with mild soap and warm water and rinse thoroughly. Gently dry by patting or blotting with toilet tissue or a soft cloth before application of this product.
  - For external hemorrhoids, apply a small amount of ointment directly to the affected area up to 4 times daily.
  - FOR INTRARECTAL USE (internal hemorrhoids): Attach applicator to tube. Lubricate applicator well, then gently insert applicator into the rectum. Squeeze a small amount (2 g) of the ointment into the rectum. Remove and discard used applicator. Apply to the affected area up to 4 times daily.

- children under 12 years of age: consult a doctor.

Other information
keep container tightly closed
store at room temperature 20 - 25 C (68 - 77 F)
do not use if the physical properties of this product have changed

INACTIVE INGREDIENT

Inactive ingredientsAmber, callicarpa nudiflora leaf, corydalis yanhusuo tuber, lanolin, panax notoginseng root, pearl, sanguisorba officinalis root, scutellaria baicalensis root, sodium borate, and styphnolobium japonicum flower.

Questions or comments?(888) 221-3496 M-F 9 am to 5 pm

PACKAGE LABEL

FARGELIN HEMORRHOIDAL OINTMENT

NDC 55614-610-01

0.705 oz (20 g)